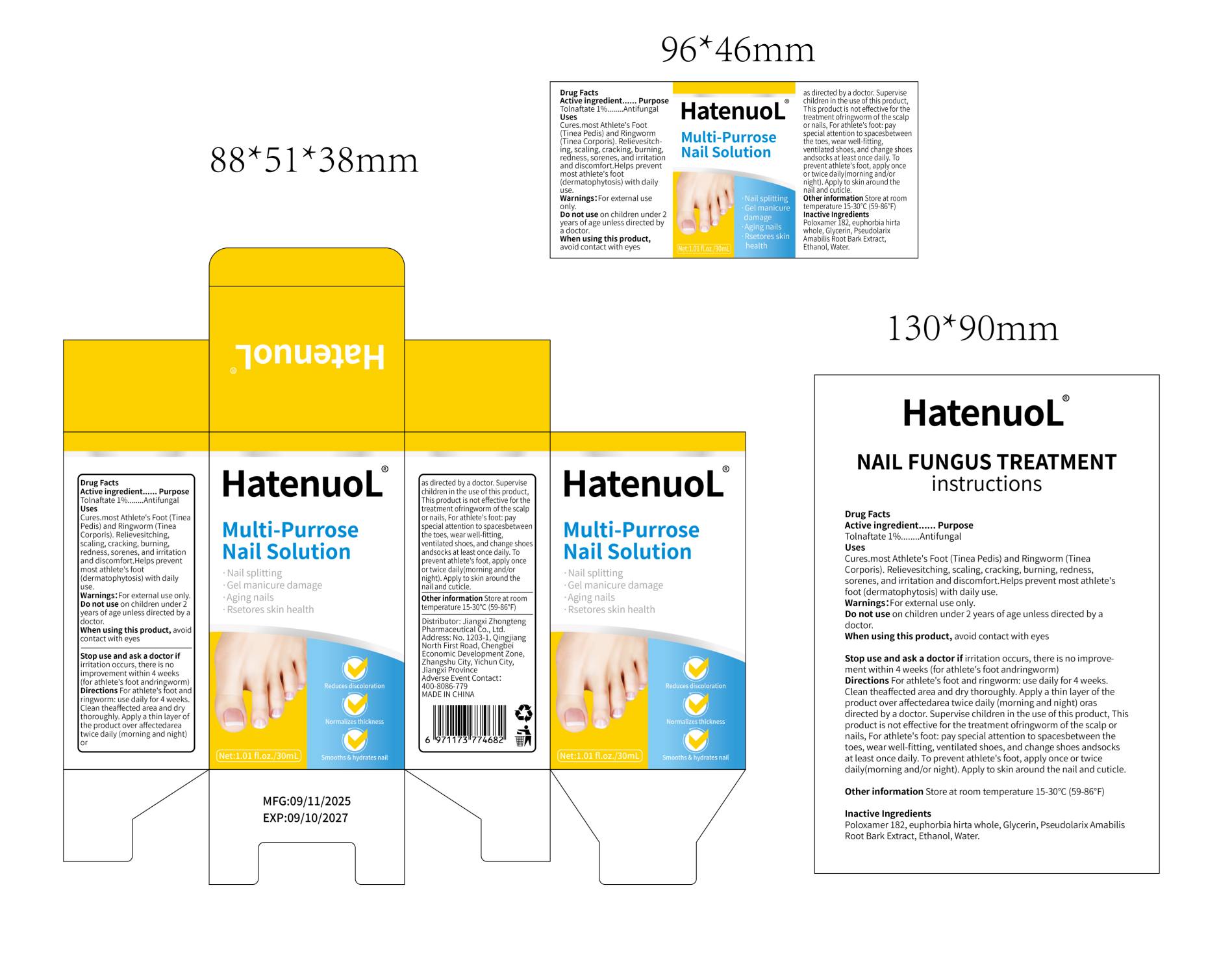 DRUG LABEL: Multi-Purrose Nail
NDC: 87240-364 | Form: SOLUTION
Manufacturer: Jiangxi Zhongteng Pharmaceutical Co., Ltd
Category: homeopathic | Type: HUMAN OTC DRUG LABEL
Date: 20251120

ACTIVE INGREDIENTS: TOLNAFTATE 1 g/1 1
INACTIVE INGREDIENTS: 2-(1-AZIRIDINYL)ETHANOL; EUPHORBIA HIRTA WHOLE; GLYCERIN; WATER; POLOXAMER 182

WARNINGS

on children under 2 years of age unless directed by a doctor

PURPOSE

Nail splitting,Gel manicure damage,Aging nails,Rsetores skin health

keep out of reach of children section

INDICATIONS AND USAGE

to prevent athlete's foot,apply once or twice daily(morning and/or night)

nail splitting,gel manicure damage,aging nails,rsetores skin health

DOSAGE AND ADMINISTRATION

to prevent athlete's foot,apply once or twice daily(morning and/or night)

ACTIVE INGREDIENT

Tolnaftate

INACTIVE INGREDIENT

water,Glycerin